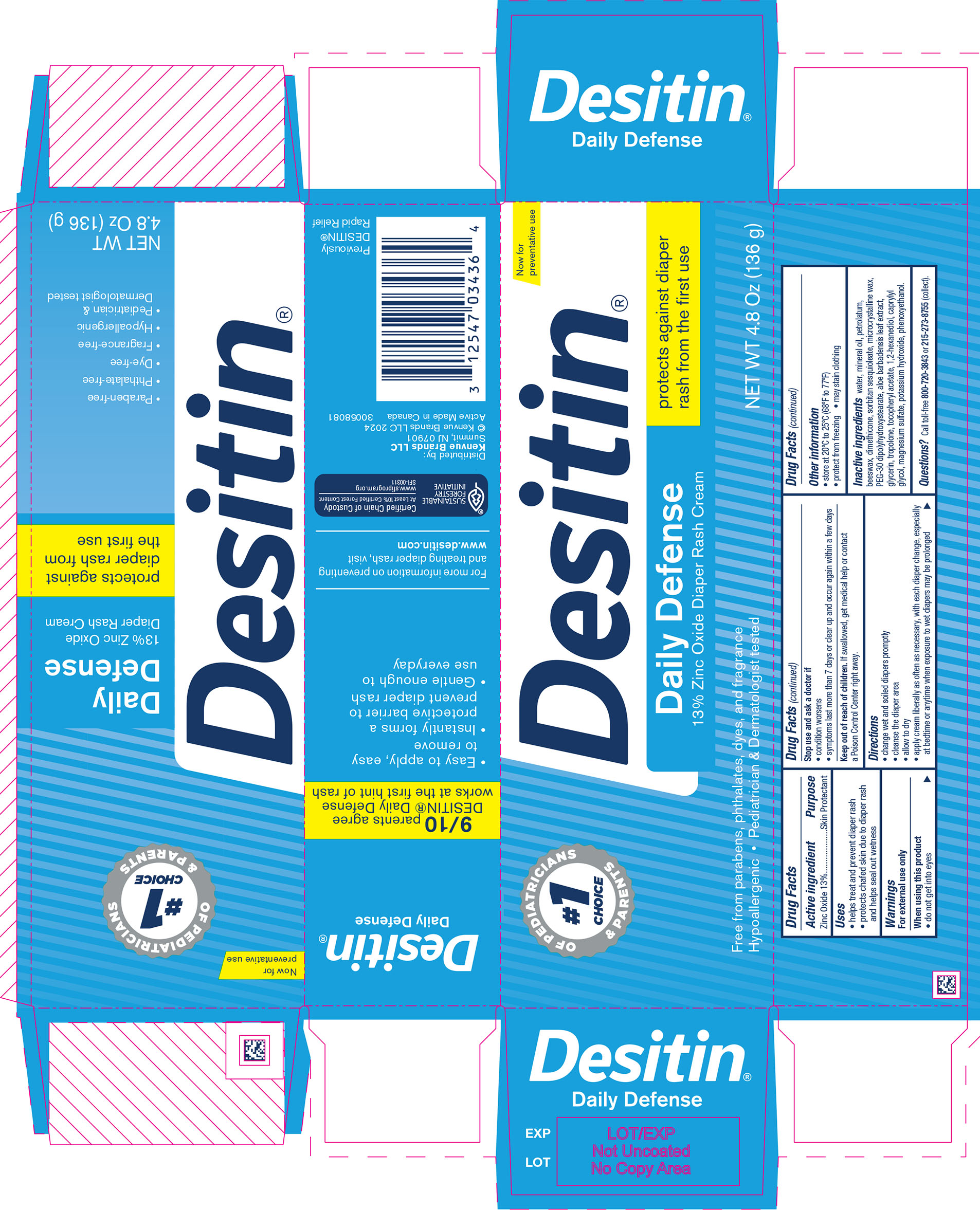 DRUG LABEL: Desitin Daily Defense Zinc Oxide Diaper Rash
NDC: 69968-0603 | Form: CREAM
Manufacturer: Kenvue Brands LLC
Category: otc | Type: HUMAN OTC DRUG LABEL
Date: 20241211

ACTIVE INGREDIENTS: ZINC OXIDE 130 mg/1 g
INACTIVE INGREDIENTS: WATER; MINERAL OIL; PETROLATUM; YELLOW WAX; DIMETHICONE; SORBITAN SESQUIOLEATE; MICROCRYSTALLINE WAX; PEG-30 DIPOLYHYDROXYSTEARATE (4000 MW); ALOE VERA LEAF; GLYCERIN; TROPOLONE; .ALPHA.-TOCOPHEROL ACETATE; 1,2-HEXANEDIOL; CAPRYLYL GLYCOL; MAGNESIUM SULFATE, UNSPECIFIED FORM; POTASSIUM HYDROXIDE; PHENOXYETHANOL

Desitin® Daily Defense Zinc Oxide Diaper Rash Cream

Drug Facts

Active ingredient

Zinc Oxide 13%

Purpose

Skin Protectant

Uses

- helps treat and prevent diaper rash
- protects chafed skin due to diaper rash and helps seal out wetness

Warnings

For external use only

When using this product

- do not get into eyes

Stop use and ask a doctor if

- condition worsens
- symptoms last more than 7 days or clear up and occur again within a few days

Keep out of reach of children. If swallowed, get medical help or contact a Poison Control Center right away.

Directions

- change wet and soiled diapers promptly
- cleanse the diaper area
- allow to dry
- apply cream liberally as often as necessary, with each diaper change, especially at bedtime or anytime when exposure to wet diapers may be prolonged

Other Information

- store at 20° to 25°C (68°F to 77°F)
- protect from freezing
- may stain clothing

Inactive ingredients

water, mineral oil, petrolatum, beeswax, dimethicone, sorbitan sesquioleate, microcrystalline wax, PEG-30 dipolyhydroxystearate, aloe barbadensis leaf extract, glycerin, tropolone, tocopheryl acetate, 1,2-hexanediol, caprylyl glycol, magnesium sulfate, potassium hydroxide, phenoxyethanol

Questions?

Call toll-free 800-720-3843 or 215-273-8755 (collect)

Distributed by:
Kenvue Brands LLC
Summit, NJ 07901

PRINCIPAL DISPLAY PANEL - 136 g Jar Label

#1
CHOICE
OF PEDIATRICIANS & PARENTS

Desitin®

Daily Defense
13% Zinc Oxide Diaper Rash Cream

protects against diaper
rash from the first use

Free from parabens, phthalates, dyes and fragrance,
Hypoallergic • Pediatrician & Dermatologist tested

NET WT 4.8 Oz (136 g)